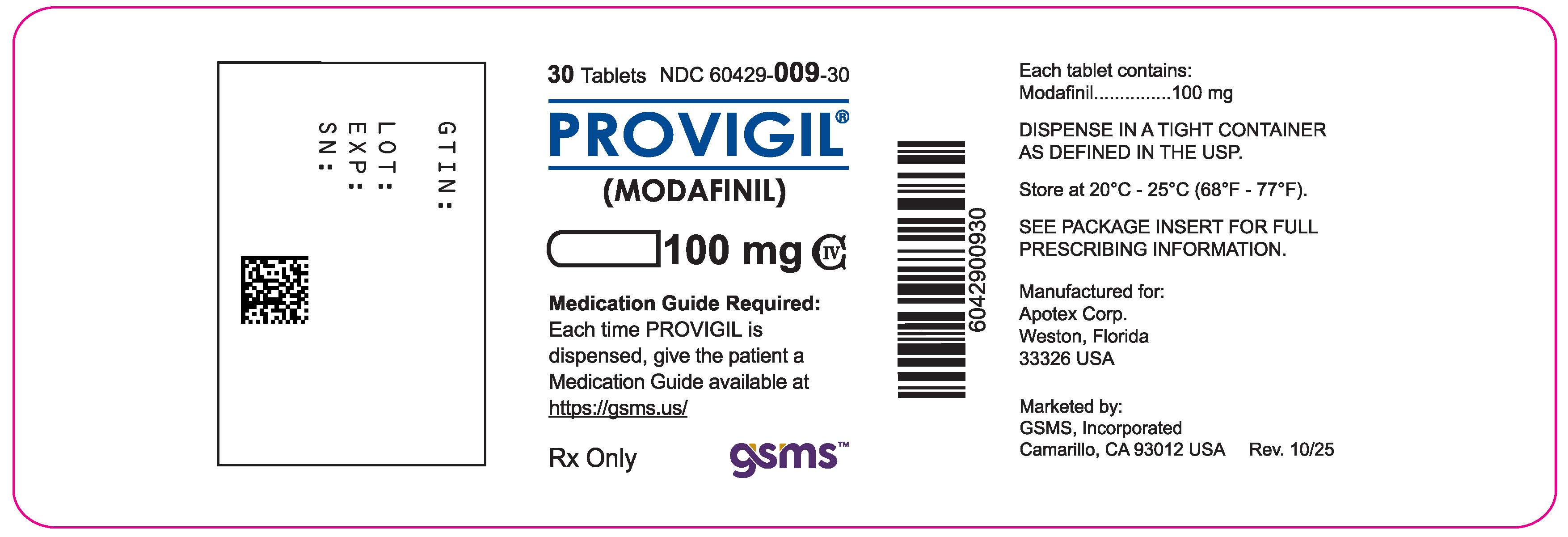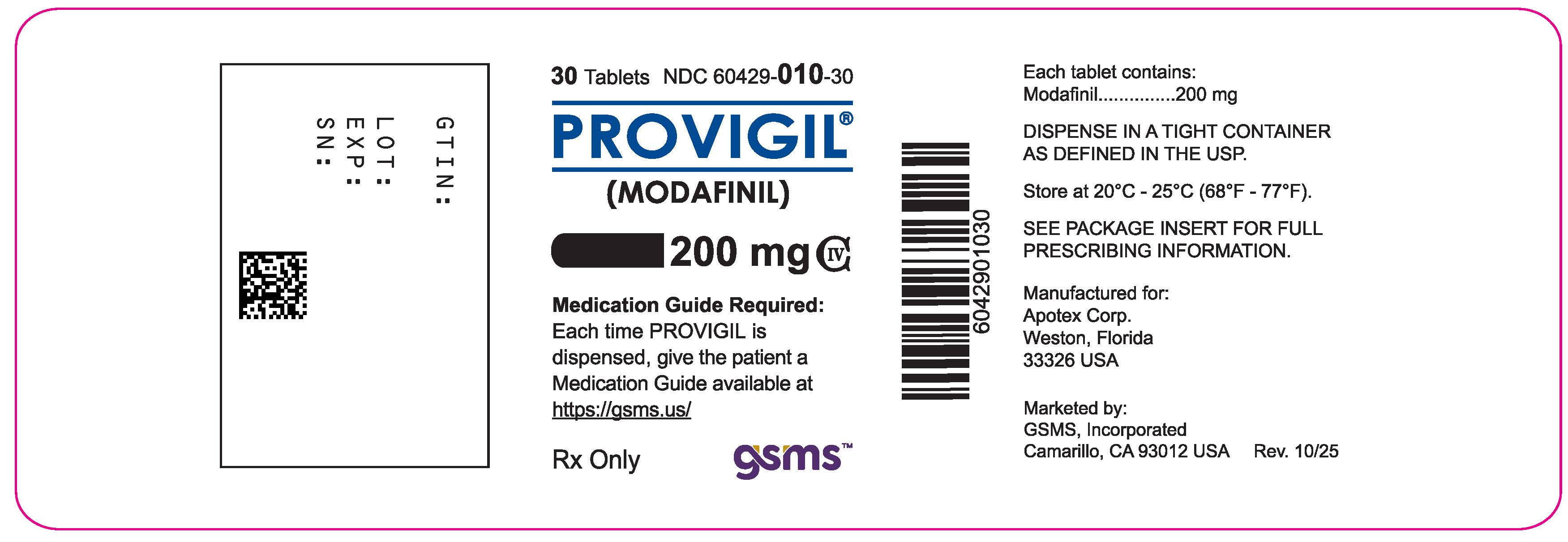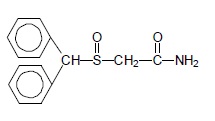 DRUG LABEL: Provigil
NDC: 60429-009 | Form: TABLET
Manufacturer: Golden State Medical Supply, Inc.
Category: prescription | Type: HUMAN PRESCRIPTION DRUG LABEL
Date: 20251016
DEA Schedule: CIV

ACTIVE INGREDIENTS: MODAFINIL 100 mg/1 1
INACTIVE INGREDIENTS: CROSCARMELLOSE SODIUM; LACTOSE MONOHYDRATE; MAGNESIUM STEARATE; MICROCRYSTALLINE CELLULOSE; POVIDONE K30; STARCH, CORN; WATER

HIGHLIGHTS OF PRESCRIBING INFORMATION

PROVIGIL tablets. These highlights do not include all the information needed to use PROVIGIL safely and effectively. See full prescribing information for PROVIGIL.
PROVIGIL®(modafinil) tablets, for oral use, C-IV
Initial U.S. Approval: 1998

1 INDICATIONS AND USAGE

PROVIGIL is indicated to improve wakefulness in adult patients with excessive sleepiness associated with narcolepsy, obstructive sleep apnea (OSA), or shift work disorder (SWD). (1)

Limitations of Use
In OSA, PROVIGIL is indicated to treat excessive sleepiness and not as treatment for the underlying obstruction.

2 DOSAGE AND ADMINISTRATION

The recommended dosage of PROVIGIL for each indication is as follows:

- Narcolepsy or OSA: 200 mg once a day in the morning. (2.1)
- SWD: 200 mg once a day, taken approximately one hour prior to start of the work shift. (2.2)
- Severe Hepatic Impairment: reduce dose to half the recommended dose. (2.3, 12.3)
- Geriatric Patients: consider lower dose. (2.4, 12.3)

3 DOSAGE FORMS AND STRENGTHS

Tablets: 100 mg and 200 mg. (3)

4 CONTRAINDICATIONS

PROVIGIL is contraindicated in patients with known hypersensitivity to modafinil or armodafinil. (4)

5 WARNINGS AND PRECAUTIONS

- Serious Rash, including Stevens-Johnson Syndrome: Discontinue PROVIGIL at the first sign of rash, unless the rash is clearly not drug-related. (5.1)
- Angioedema and Anaphylaxis Reactions: If suspected, discontinue PROVIGIL. (5.2)
- Multi-organ Hypersensitivity Reactions: If suspected, discontinue PROVIGIL. (5.3)
- Persistent Sleepiness: Assess patients frequently for degree of sleepiness and, if appropriate, advise patients to avoid driving or engaging in any other potentially dangerous activity. (5.4)
- Psychiatric Symptoms: Use caution in patients with a history of psychosis, depression, or mania. Consider discontinuing PROVIGIL if psychiatric symptoms develop. (5.5)
- Known Cardiovascular Disease: Consider increased monitoring. (5.7)

6 ADVERSE REACTIONS

Most common adverse reactions (≥5%): headache, nausea, nervousness, rhinitis, diarrhea, back pain, anxiety, insomnia, dizziness, and dyspepsia. (6.1)

To report SUSPECTED ADVERSE REACTIONS, contact Apotex Corp. at 1-800-706-5575 or FDA at 1-800-FDA-1088 or www.fda.gov/medwatch.

7 DRUG INTERACTIONS

- Steroidal contraceptives (e.g., ethinyl estradiol): Use alternative or concomitant methods of contraception while taking PROVIGIL and for one month after discontinuation of PROVIGIL treatment. (7)
- Cyclosporine: Blood concentrations of cyclosporine may be reduced. (7)
- CYP2C19 substrates, such as omeprazole, phenytoin, and diazepam: Exposure of these medications may be increased. (7)

8 USE IN SPECIFIC POPULATIONS

Pregnancy: Based on animal data, may cause fetal harm. (8.1)

FULL PRESCRIBING INFORMATION

1 INDICATIONS AND USAGE

PROVIGIL is indicated to improve wakefulness in adult patients with excessive sleepiness associated with narcolepsy, obstructive sleep apnea (OSA), or shift work disorder (SWD).

Limitations of Use

In OSA, PROVIGIL is indicated to treat excessive sleepiness and not as treatment for the underlying obstruction. If continuous positive airway pressure (CPAP) is the treatment of choice for a patient, a maximal effort to treat with CPAP for an adequate period of time should be made prior to initiating and during treatment with PROVIGIL for excessive sleepiness.

2 DOSAGE AND ADMINISTRATION

2.1 Dosage in Narcolepsy and Obstructive Sleep Apnea (OSA)

The recommended dosage of PROVIGIL for patients with narcolepsy or OSA is 200 mg taken orally once a day as a single dose in the morning.

Doses up to 400 mg/day, given as a single dose, have been well tolerated, but there is no consistent evidence that this dose confers additional benefit beyond that of the 200 mg/day dose [see Clinical Pharmacology (12.3) and Clinical Studies (14.1, 14.2)] .

2.2 Dosage in Shift Work Disorder (SWD)

The recommended dosage of PROVIGIL for patients with SWD is 200 mg taken orally once a day as a single dose approximately 1 hour prior to the start of their work shift .

2.3 Dosage Modifications in Patients with Severe Hepatic Impairment

In patients with severe hepatic impairment, the dosage of PROVIGIL should be reduced to one-half of that recommended for patients with normal hepatic function [see Use in Specific Populations (8.6) and Clinical Pharmacology (12.3)] .

2.4 Use in Geriatric Patients

Consideration should be given to the use of lower doses and close monitoring in geriatric patients [see Use in Specific Populations (8.5)] .

3 DOSAGE FORMS AND STRENGTHS

- 100 mg – capsule-shaped, white to off white, tablet, debossed with "PROVIGIL" on one side and "100 MG" on the other.
- 200 mg – capsule-shaped, white to off white, scored, tablet, debossed with "PROVIGIL" on one side and "200 MG" on the other.

4 CONTRAINDICATIONS

PROVIGIL is contraindicated in patients with known hypersensitivity to modafinil or armodafinil or its inactive ingredients [see Warnings and Precautions (5.1, 5.2, 5.3)] .

5 WARNINGS AND PRECAUTIONS

5.1 Serious Rash, including Stevens-Johnson Syndrome

Serious rash requiring hospitalization and discontinuation of treatment has been reported in association with the use of modafinil.

In clinical trials of modafinil, the incidence of rash resulting in discontinuation was approximately 0.8% (13 per 1,585) in pediatric patients (age <17 years); these rashes included 1 case of possible Stevens-Johnson Syndrome (SJS) and 1 case of apparent multi-organ hypersensitivity reaction. Several of the cases were associated with fever and other abnormalities (e.g., vomiting, leukopenia). The median time to rash that resulted in discontinuation was 13 days. No such cases were observed among 380 pediatric patients who received placebo. PROVIGIL is not approved for use in pediatric patients for any indication [see Use in Specific Populations (8.4)] .

Rare cases of serious or life-threatening rash, including SJS, Toxic Epidermal Necrolysis (TEN), and Drug Rash with Eosinophilia and Systemic Symptoms (DRESS) have been reported in adults and children in worldwide postmarketing experience. The reporting rate of TEN and SJS associated with modafinil use, which is generally accepted to be an underestimate due to underreporting, exceeds the background incidence rate. Estimates of the background incidence rate for these serious skin reactions in the general population range between 1 to 2 cases per million-person years.

There are no factors that are known to predict the risk of occurrence or the severity of rash associated with PROVIGIL. Nearly all cases of serious rash associated with modafinil occurred within 1 to 5 weeks after treatment initiation. However, isolated cases have been reported after prolonged treatment (e.g., 3 months). Accordingly, duration of therapy cannot be relied upon as a means to predict the potential risk heralded by the first appearance of a rash.

Although benign rashes also occur with PROVIGIL, it is not possible to reliably predict which rashes will prove to be serious. Accordingly, PROVIGIL should be discontinued at the first sign of rash, unless the rash is clearly not drug-related. Discontinuation of treatment may not prevent a rash from becoming life-threatening or permanently disabling or disfiguring.

5.2 Angioedema and Anaphylaxis Reactions

Angioedema and hypersensitivity (with rash, dysphagia, and bronchospasm), were observed in patients treated with armodafinil, the R enantiomer of modafinil (which is the racemic mixture). No such cases were observed in modafinil clinical trials. However, angioedema has been reported in postmarketing experience with modafinil. Patients should be advised to discontinue therapy and immediately report to their physician any signs or symptoms suggesting angioedema or anaphylaxis (e.g., swelling of face, eyes, lips, tongue or larynx; difficulty in swallowing or breathing; hoarseness).

5.3 Multi-organ Hypersensitivity Reactions

Multi-organ hypersensitivity reactions, including at least one fatality in postmarketing experience, have occurred in close temporal association (median time to detection 13 days: range 4-33) to the initiation of modafinil.

Although there have been a limited number of reports, multi-organ hypersensitivity reactions may result in hospitalization or be life-threatening. There are no factors that are known to predict the risk of occurrence or the severity of multi-organ hypersensitivity reactions. Signs and symptoms of this disorder were diverse; however, patients typically, although not exclusively, presented with fever and rash associated with other organ system involvement. Other associated manifestations included myocarditis, hepatitis, liver function test abnormalities, hematological abnormalities (e.g., eosinophilia, leukopenia, thrombocytopenia), pruritus, and asthenia. Because multi-organ hypersensitivity is variable in its expression, other organ system symptoms and signs, not noted here, may occur.

If a multi-organ hypersensitivity reaction is suspected, PROVIGIL should be discontinued. Although there are no case reports to indicate cross‑sensitivity with other drugs that produce this syndrome, the experience with drugs associated with multi-organ hypersensitivity would indicate this to be a possibility.

5.4 Persistent Sleepiness

Patients with abnormal levels of sleepiness who take PROVIGIL should be advised that their level of wakefulness may not return to normal. Patients with excessive sleepiness, including those taking PROVIGIL, should be frequently reassessed for their degree of sleepiness and, if appropriate, advised to avoid driving or any other potentially dangerous activity. Prescribers should also be aware that patients may not acknowledge sleepiness or drowsiness until directly questioned about drowsiness or sleepiness during specific activities.

5.5 Psychiatric Symptoms

Psychiatric adverse reactions have been reported in patients treated with modafinil.

In the adult PROVIGIL controlled trials, psychiatric symptoms resulting in treatment discontinuation (at a frequency ≥0.3%) and reported more often in patients treated with PROVIGIL compared to those treated with placebo were anxiety (1%), nervousness (1%), insomnia (<1%), confusion (<1%), agitation (<1%), and depression (<1%).

Postmarketing adverse reactions associated with the use of modafinil have included mania, delusions, hallucinations, suicidal ideation, and aggression, some resulting in hospitalization. Many, but not all, patients had a prior psychiatric history. One healthy male volunteer developed ideas of reference, paranoid delusions, and auditory hallucinations in association with multiple daily 600 mg doses of PROVIGIL (three times the recommended dose) and sleep deprivation. There was no evidence of psychosis 36 hours after drug discontinuation.

Caution should be exercised when PROVIGIL is given to patients with a history of psychosis, depression, or mania. Consideration should be given to the possible emergence or exacerbation of psychiatric symptoms in patients treated with PROVIGIL. If psychiatric symptoms develop in association with PROVIGIL administration, consider discontinuing PROVIGIL.

5.6 Effects on Ability to Drive and Use Machinery

Although PROVIGIL has not been shown to produce functional impairment, any drug affecting the CNS may alter judgment, thinking or motor skills. Patients should be cautioned about operating an automobile or other hazardous machinery until it is reasonably certain that PROVIGIL therapy will not adversely affect their ability to engage in such activities.

5.7 Cardiovascular Events

In modafinil clinical studies, cardiovascular adverse reactions, including chest pain, palpitations, dyspnea, and transient ischemic T-wave changes on ECG occurred in three subjects in association with mitral valve prolapse or left ventricular hypertrophy. In a Canadian clinical trial, a 35 year old obese narcoleptic male with a prior history of syncopal episodes experienced a 9-second episode of asystole after 27 days of modafinil treatment (300 mg/day in divided doses). PROVIGIL is not recommended in patients with a history of left ventricular hypertrophy or in patients with mitral valve prolapse who have experienced the mitral valve prolapse syndrome when previously receiving CNS stimulants. Findings suggestive of mitral valve prolapse syndrome include but are not limited to ischemic ECG changes, chest pain, or arrhythmia. If new onset of any of these findings occurs, consider cardiac evaluation. Consider increased monitoring in patients with a recent history of myocardial infarction or unstable angina.

Blood pressure monitoring in short term (≤ 3 months) controlled trials showed no clinically significant changes in mean systolic and diastolic blood pressure in patients receiving PROVIGIL as compared to placebo. However, a retrospective analysis of the use of antihypertensive medication in these studies showed that a greater proportion of patients on PROVIGIL required new or increased use of antihypertensive medications (2.4%) compared to patients on placebo (0.7%). The differential use was slightly larger when only studies in OSA were included, with 3.4% of patients on PROVIGIL and 1.1% of patients on placebo requiring such alterations in the use of antihypertensive medication. Increased monitoring of heart rate and blood pressure may be appropriate in patients on PROVIGIL. Caution should be exercised when prescribing PROVIGIL to patients with known cardiovascular disease.

6 ADVERSE REACTIONS

The following serious adverse reactions are described elsewhere in the labeling:

- Serious Rash, including Stevens-Johnson Syndrome [see Warnings and Precautions (5.1)]
- Angioedema and Anaphylaxis Reactions [see Warnings and Precautions (5.2)]
- Multi-organ Hypersensitivity Reactions [see Warnings and Precautions (5.3)]
- Persistent Sleepiness [see Warnings and Precautions (5.4)]
- Psychiatric Symptoms [see Warnings and Precautions (5.5)]
- Effects on Ability to Drive and Use Machinery [see Warnings and Precautions (5.6)]
- Cardiovascular Events [see Warnings and Precautions (5.7)]

6.1 Clinical Trials Experience

Because clinical trials are conducted under widely varying conditions, adverse reaction rates observed in the clinical trials of a drug cannot be directly compared to rates in the clinical trials of another drug and may not reflect the rates observed in practice.

PROVIGIL has been evaluated for safety in over 3,500 patients, of whom more than 2,000 patients with excessive sleepiness associated with OSA, SWD, and narcolepsy.

Most Common Adverse Reactions

In placebo-controlled clinical trials, the most common adverse reactions (≥ 5%) associated with the use of PROVIGIL more frequently than placebo-treated patients were headache, nausea, nervousness, rhinitis, diarrhea, back pain, anxiety, insomnia, dizziness, and dyspepsia. The adverse reaction profile was similar across these studies.

Table 1 presents the adverse reactions that occurred at a rate of 1% or more and were more frequent in PROVIGIL-treated patients than in placebo-treated patients in the placebo-controlled clinical trials.

Table 1. Adverse Reactions in Pooled Placebo-Controlled Trials [Adverse Reactions that occurred in > 1% of PROVIGIL-treated patients (either 200, 300, or 400 mg once daily) and greater incidence than placebo] in Narcolepsy, OSA, and SWD
 | PROVIGIL (%) (n = 934) | Placebo (%) (n = 567)
Headache | 34 | 23
Nausea | 11 | 3
Nervousness | 7 | 3
Rhinitis | 7 | 6
Back Pain | 6 | 5
Diarrhea | 6 | 5
Anxiety | 5 | 1
Dizziness | 5 | 4
Dyspepsia | 5 | 4
Insomnia | 5 | 1
Anorexia | 4 | 1
Dry Mouth | 4 | 2
Pharyngitis | 4 | 2
Chest Pain | 3 | 1
Hypertension | 3 | 1
Abnormal Liver Function | 2 | 1
Constipation | 2 | 1
Depression | 2 | 1
Palpitation | 2 | 1
Paresthesia | 2 | 0
Somnolence | 2 | 1
Tachycardia | 2 | 1
Vasodilatation | 2 | 0
Abnormal Vision | 1 | 0
Agitation | 1 | 0
Asthma | 1 | 0
Chills | 1 | 0
Confusion | 1 | 0
Dyskinesia | 1 | 0
Edema | 1 | 0
Emotional Lability | 1 | 0
Eosinophilia | 1 | 0
Epistaxis | 1 | 0
Flatulence | 1 | 0
Hyperkinesia | 1 | 0
Hypertonia | 1 | 0
Mouth Ulceration | 1 | 0
Sweating | 1 | 0
Taste Perversion | 1 | 0
Thirst | 1 | 0
Tremor | 1 | 0
Urine Abnormality | 1 | 0
Vertigo | 1 | 0

Dose-Dependent Adverse Reactions

In the placebo-controlled clinical trials which compared doses of 200, 300, and 400 mg/day of PROVIGIL and placebo, the following adverse reactions were dose related: headache and anxiety.

Adverse Reactions Resulting in Discontinuation of Treatment

In placebo-controlled clinical trials, 74 of the 934 patients (8%) who received PROVIGIL discontinued due to an adverse reaction compared to 3% of patients that received placebo. The most frequent reasons for discontinuation that occurred at a higher rate for PROVIGIL than placebo patients were headache (2%), nausea, anxiety, dizziness, insomnia, chest pain, and nervousness (each <1%).

Laboratory Abnormalities

Clinical chemistry, hematology, and urinalysis parameters were monitored in the studies. Mean plasma levels of gamma glutamyltransferase (GGT) and alkaline phosphatase (AP) were found to be higher following administration of PROVIGIL, but not placebo. Few patients, however, had GGT or AP elevations outside of the normal range. Shifts to higher, but not clinically significantly abnormal, GGT and AP values appeared to increase with time in the population treated with PROVIGIL in the placebo-controlled clinical trials. No differences were apparent in alanine aminotransferase (ALT), aspartate aminotransferase (AST), total protein, albumin, or total bilirubin.

6.2 Postmarketing Experience

The following adverse reactions have been identified during post approval use of PROVIGIL. Because these reactions are reported voluntarily from a population of uncertain size, it is not always possible to reliably estimate their frequency or establish a causal relationship to drug exposure.

Hematologic: agranulocytosis

Psychiatric disorders: psychomotor hyperactivity

7 DRUG INTERACTIONS

Effects of PROVIGIL on CYP3A4/5 Substrates

The clearance of drugs that are substrates for CYP3A4/5 (e.g., steroidal contraceptives, cyclosporine, midazolam, and triazolam) may be increased by PROVIGIL via induction of metabolic enzymes, which results in lower systemic exposure. Dosage adjustment of these drugs should be considered when these drugs are used concomitantly with PROVIGIL [see Clinical Pharmacology (12.3)] .

The effectiveness of steroidal contraceptives may be reduced when used with PROVIGIL and for one month after discontinuation of therapy. Alternative or concomitant methods of contraception are recommended for patients taking steroidal contraceptives (e.g., ethinyl estradiol) when treated concomitantly with PROVIGIL and for one month after discontinuation of PROVIGIL treatment.

Blood levels of cyclosporine may be reduced when used with PROVIGIL. Monitoring of circulating cyclosporine concentrations and appropriate dosage adjustment for cyclosporine should be considered when used concomitantly with PROVIGIL.

Effects of PROVIGIL on CYP2C19 Substrates

Elimination of drugs that are substrates for CYP2C19 (e.g., phenytoin, diazepam, propranolol, omeprazole, and clomipramine) may be prolonged by PROVIGIL via inhibition of metabolic enzymes, with resultant higher systemic exposure. In individuals deficient in the CYP2D6 enzyme, the levels of CYP2D6 substrates which have ancillary routes of elimination through CYP2C19, such as tricyclic antidepressants and selective serotonin reuptake inhibitors, may be increased by co-administration of PROVIGIL. Dose adjustments of these drugs and other drugs that are substrates for CYP2C19 may be necessary when used concomitantly with PROVIGIL [see Clinical Pharmacology (12.3)] .

Warfarin

More frequent monitoring of prothrombin times/INR should be considered whenever PROVIGIL is coadministered with warfarin [see Clinical Pharmacology (12.3)] .

Monoamine Oxidase (MAO) Inhibitors

Caution should be used when concomitantly administering MAO inhibitors and PROVIGIL.

8 USE IN SPECIFIC POPULATIONS

8.1 Pregnancy

Pregnancy Category C

There are no adequate and well-controlled studies of modafinil in pregnant women. Intrauterine growth restriction and spontaneous abortion have been reported in association with modafinil (a mixture of R- and S-modafinil) and armodafinil (the R-enantiomer of modafinil). Although the pharmacology of modafinil is not identical to that of the sympathomimetic amines, it does share some pharmacologic properties with this class. Certain of these drugs have been associated with intrauterine growth restriction and spontaneous abortions. Whether the cases reported with modafinil are drug-related is unknown. In studies of modafinil and armodafinil conducted in rats (modafinil, armodafinil) and rabbits (modafinil), developmental toxicity was observed at clinically relevant plasma exposures. PROVIGIL should be used during pregnancy only if the potential benefit justifies the potential risk to the fetus.

Modafinil (50, 100, or 200 mg/kg/day) administered orally to pregnant rats throughout organogenesis caused, in the absence of maternal toxicity, an increase in resorptions and an increased incidence of visceral and skeletal variations in the offspring at the highest dose tested. The higher no-effect dose for embryofetal developmental toxicity in rats (100 mg/kg/day) was associated with a plasma modafinil AUC less than that in humans at the recommended human dose (RHD) of PROVIGIL (200 mg/day). However, in a subsequent study of up to 480 mg/kg/day of modafinil, no adverse effects on embryofetal development were observed. Oral administration of armodafinil (60, 200, or 600 mg/kg/day) to pregnant rats throughout organogenesis resulted in increased incidences of fetal visceral and skeletal variations and decreased fetal body weight at the highest dose tested. The highest no-effect dose for embryofetal developmental toxicity in rats (200 mg/kg/day) was associated with a plasma armodafinil AUC less than that in humans at the RHD of PROVIGIL.

Modafinil administered orally to pregnant rabbits throughout organogenesis at doses of up to 100 mg/kg/day had no effect on embryofetal development; however, the doses used were too low to adequately assess the effects of modafinil on embryofetal development. In a subsequent developmental toxicity study evaluating doses of 45, 90, and 180 mg/kg/day in pregnant rabbits, the incidences of fetal structural alterations and embryofetal death were increased at the highest dose. The highest no-effect dose for developmental toxicity (100 mg/kg/day) was associated with a plasma modafinil AUC similar to that in humans at the RHD of PROVIGIL.

Modafinil administration to rats throughout gestation and lactation at oral doses of up to 200 mg/kg/day resulted in decreased viability in the offspring at doses greater than 20 mg/kg/day, a dose resulting in a plasma modafinil AUC less than that in humans at the RHD of PROVIGIL. No effects on postnatal developmental and neurobehavioral parameters were observed in surviving offspring.

Pregnancy Registry

A pregnancy registry has been established to collect information on the pregnancy outcomes of women exposed to PROVIGIL. Healthcare providers are encouraged to register pregnant patients, or pregnant women may enroll themselves in the registry by calling 1-866-404-4106 (toll free).

8.3 Nursing Mothers

It is not known whether modafinil or its metabolites are excreted in human milk. Because many drugs are excreted in human milk, caution should be exercised when PROVIGIL is administered to a nursing woman.

8.4 Pediatric Use

Safety and effectiveness in pediatric patients have not been established. PROVIGIL is not approved in this population for any indication.

Serious skin rashes, including erythema multiforme major (EMM) and Stevens-Johnson Syndrome (SJS) have been associated with modafinil use in pediatric patients [see Warnings and Precautions (5.1)] .

In a controlled 6-week study, 165 pediatric patients (aged 5-17 years) with narcolepsy were treated with modafinil (n=123), or placebo (n=42). There were no statistically significant differences favoring modafinil over placebo in prolonging sleep latency as measured by MSLT, or in perceptions of sleepiness as determined by the clinical global impression-clinician scale (CGI-C).

In the controlled and open-label clinical studies, treatment emergent adverse reactions of the psychiatric and nervous system included Tourette’s syndrome, insomnia, hostility, increased cataplexy, increased hypnagogic hallucinations, and suicidal ideation. Transient leukopenia, which resolved without medical intervention, was also observed. In the controlled clinical study, 3 of 38 girls, ages 12 or older, treated with modafinil experienced dysmenorrhea compared to 0 of 10 girls who received placebo.

There were three 7 to 9 week, double-blind, placebo-controlled, parallel group studies in children and adolescents (aged 6-17 years) with Attention-Deficit Hyperactivity Disorder (ADHD). Two of the studies were flexible-dose studies (up to 425 mg/day), and the third was a fixed-dose study (340 mg/day for patients <30 kg and 425 mg/day for patients ≥30 kg). Although these studies showed statistically significant differences favoring modafinil over placebo in reducing ADHD symptoms as measured by the ADHD-RS (school version), there were 3 cases of serious rash including one case of possible SJS among 933 patients exposed to modafinil in this program. Modafinil is not approved for use in treating ADHD.

8.5 Geriatric Use

In clinical trials, experience in a limited number of modafinil-treated patients who were greater than 65 years of age showed an incidence of adverse reactions similar to other age groups. In elderly patients, elimination of modafinil and its metabolites may be reduced as a consequence of aging. Therefore, consideration should be given to the use of lower doses and close monitoring in this population [see Dosage and Administration (2.4) and Clinical Pharmacology (12.3)].

8.6 Hepatic Impairment

In patients with severe hepatic impairment, the dose of PROVIGIL should be reduced to one-half of that recommended for patients with normal hepatic function [see Dosage and Administration (2.3) and Clinical Pharmacology (12.3)] .

9 DRUG ABUSE AND DEPENDENCE

9.1 Controlled Substance

PROVIGIL contains modafinil, a Schedule IV controlled substance.

9.2 Abuse

In humans, modafinil produces psychoactive and euphoric effects, alterations in mood, perception, thinking, and feelings typical of other CNS stimulants. In in vitro binding studies, modafinil binds to the dopamine reuptake site and causes an increase in extracellular dopamine, but no increase in dopamine release. Modafinil is reinforcing, as evidenced by its self-administration in monkeys previously trained to self-administer cocaine. In some studies, modafinil was also partially discriminated as stimulant-like. Physicians should follow patients closely, especially those with a history of drug and/or stimulant (e.g., methylphenidate, amphetamine, or cocaine) abuse. Patients should be observed for signs of misuse or abuse (e.g., incrementation of doses or drug-seeking behavior).

The abuse potential of modafinil (200, 400, and 800 mg) was assessed relative to methylphenidate (45 and 90 mg) in an inpatient study in individuals experienced with drugs of abuse. Results from this clinical study demonstrated that modafinil produced psychoactive and euphoric effects and feelings consistent with other scheduled CNS stimulants (methylphenidate).

9.3 Dependence

In one placebo-controlled clinical trial, the effects of modafinil withdrawal were monitored following 9 weeks of modafinil use. There were no reported withdrawal symptoms with modafinil during 14 days of observation, although sleepiness returned in narcoleptic patients.

10 OVERDOSAGE

In clinical trials, a total of 151 protocol-specified doses ranging from 1000 to 1600 mg/day (5 to 8 times the recommended daily dose of PROVIGIL) have been administered to 32 subjects, including 13 subjects who received doses of 1000 or 1200 mg/day for 7 to 21 consecutive days. In addition, several intentional acute overdoses occurred; the two largest being 4500 mg and 4000 mg taken by two subjects participating in foreign depression studies. None of these study subjects experienced any unexpected or life-threatening effects. Adverse reactions that were reported at these doses included excitation or agitation, insomnia, and slight or moderate elevations in hemodynamic parameters. Other observed high-dose effects in clinical studies have included anxiety, irritability, aggressiveness, confusion, nervousness, tremor, palpitations, sleep disturbances, nausea, diarrhea, and decreased prothrombin time.

From postmarketing experience, there have been reports of fatal overdoses involving modafinil alone or in combination with other drugs. Symptoms most often accompanying PROVIGIL overdose, alone or in combination with other drugs have included insomnia; central nervous system symptoms such as restlessness, disorientation, confusion, agitation, anxiety, excitation, and hallucination; digestive changes such as nausea and diarrhea; and cardiovascular changes such as tachycardia, bradycardia, hypertension, and chest pain.

Cases of accidental ingestion/overdose have been reported in children as young as 11 months of age. The highest reported accidental ingestion on a mg/kg basis occurred in a three-year-old boy who ingested 800-1000 mg (50-63 mg/kg) of PROVIGIL. The child remained stable. The symptoms associated with overdose in children were similar to those observed in adults.

No specific antidote exists for the toxic effects of a PROVIGIL overdose. Such overdoses should be managed with primarily supportive care, including cardiovascular monitoring.

11 DESCRIPTION

PROVIGIL (modafinil) is a wakefulness‑promoting agent for oral administration. Modafinil is a racemic compound. The chemical name for modafinil is 2‑[(diphenylmethyl)sulfinyl]acetamide. The molecular formula is C15H15NO2S and the molecular weight is 273.35.

The chemical structure is:

Modafinil is a white to off-white, crystalline powder that is practically insoluble in water and cyclohexane. It is sparingly to slightly soluble in methanol and acetone.

PROVIGIL tablets contain 100 mg or 200 mg of modafinil and the following inactive ingredients: croscarmellose sodium, lactose monohydrate, magnesium stearate, microcrystalline cellulose, povidone, and pregelatinized starch.

12 CLINICAL PHARMACOLOGY

12.1 Mechanism of Action

The mechanism(s) through which modafinil promotes wakefulness is unknown. Modafinil has wake-promoting actions similar to sympathomimetic agents including amphetamine and methylphenidate, although the pharmacologic profile is not identical to that of the sympathomimetic amines.

Modafinil-induced wakefulness can be attenuated by the α1-adrenergic receptor antagonist, prazosin; however, modafinil is inactive in other in vitro assay systems known to be responsive to α-adrenergic agonists such as the rat vas deferens preparation.

Modafinil is not a direct- or indirect-acting dopamine receptor agonist. However, in vitro, modafinil binds to the dopamine transporter and inhibits dopamine reuptake. This activity has been associated in vivo with increased extracellular dopamine levels in some brain regions of animals. In genetically engineered mice lacking the dopamine transporter (DAT), modafinil lacked wake-promoting activity, suggesting that this activity was DAT-dependent. However, the wake-promoting effects of modafinil, unlike those of amphetamine, were not antagonized by the dopamine receptor antagonist haloperidol in rats. In addition, alpha-methyl-p-tyrosine, a dopamine synthesis inhibitor, blocks the action of amphetamine, but does not block locomotor activity induced by modafinil.

In the cat, equal wakefulness-promoting doses of methylphenidate and amphetamine increased neuronal activation throughout the brain. Modafinil at an equivalent wakefulness-promoting dose selectively and prominently increased neuronal activation in more discrete regions of the brain. The relationship of this finding in cats to the effects of modafinil in humans is unknown.

In addition to its wake-promoting effects and ability to increase locomotor activity in animals, modafinil produces psychoactive and euphoric effects, alterations in mood, perception, thinking, and feelings typical of other CNS stimulants in humans. Modafinil has reinforcing properties, as evidenced by its self-administration in monkeys previously trained to self-administer cocaine; modafinil was also partially discriminated as stimulant-like.

The optical enantiomers of modafinil have similar pharmacological actions in animals. Two major metabolites of modafinil, modafinil acid and modafinil sulfone, do not appear to contribute to the CNS-activating properties of modafinil.

12.3 Pharmacokinetics

Modafinil is a 1:1 racemic compound, whose enantiomers have different pharmacokinetics (e.g., the half-life of R-modafinil is approximately three times that of S-modafinil in adult humans). The enantiomers do not interconvert. At steady state, total exposure to R-modafinil is approximately three times that for S-modafinil. The trough concentration (Cmin,ss) of circulating modafinil after once daily dosing consists of 90% of R-modafinil and 10% of S-modafinil. The effective elimination half-life of modafinil after multiple doses is about 15 hours. The enantiomers of modafinil exhibit linear kinetics upon multiple dosing of 200-600 mg/day once daily in healthy volunteers. Apparent steady states of total modafinil and R-modafinil are reached after 2-4 days of dosing.

Absorption

PROVIGIL is readily absorbed after oral administration, with peak plasma concentrations occurring at 2-4 hours. The bioavailability of PROVIGIL tablets is approximately equal to that of an aqueous suspension. The absolute oral bioavailability was not determined due to the aqueous insolubility (<1 mg/mL) of modafinil, which precluded intravenous administration. Food has no effect on overall PROVIGIL bioavailability; however, time to reach peak concentration (tmax) may be delayed by approximately one hour if taken with food.

Distribution

PROVIGIL has an apparent volume of distribution of approximately 0.9 L/kg. In human plasma, in vitro, modafinil is moderately bound to plasma protein (approximately 60%), mainly to albumin. The potential for interactions of PROVIGIL with highly protein-bound drugs is considered to be minimal.

Metabolism and Elimination

The major route of elimination is metabolism (approximately 90%), primarily by the liver, with subsequent renal elimination of the metabolites. Urine alkalinization has no effect on the elimination of modafinil.

Metabolism occurs through hydrolytic deamidation, S-oxidation, aromatic ring hydroxylation, and glucuronide conjugation. Less than 10% of an administered dose is excreted as the parent compound. In a clinical study using radiolabeled modafinil, a total of 81% of the administered radioactivity was recovered in 11 days post-dose, predominantly in the urine (80% vs. 1.0% in the feces). The largest fraction of the drug in urine was modafinil acid, but at least six other metabolites were present in lower concentrations. Only two metabolites reach appreciable concentrations in plasma, i.e., modafinil acid and modafinil sulfone. In preclinical models, modafinil acid, modafinil sulfone, 2-[(diphenylmethyl)sulfonyl]acetic acid and 4-hydroxy modafinil, were inactive or did not appear to mediate the arousal effects of modafinil.

In adults, decreases in trough levels of modafinil have sometimes been observed after multiple weeks of dosing, suggesting auto-induction, but the magnitude of the decreases and the inconsistency of their occurrence suggest that their clinical significance is minimal. Significant accumulation of modafinil sulfone has been observed after multiple doses due to its long elimination half-life of 40 hours. Auto-induction of metabolizing enzymes, most importantly cytochrome P-450 CYP3A4, has also been observed in vitro after incubation of primary cultures of human hepatocytes with modafinil and in vivo after extended administration of modafinil at 400 mg/day.

Specific Populations

Age

A slight decrease (approximately 20%) in the oral clearance (CL/F) of modafinil was observed in a single dose study at 200 mg in 12 subjects with a mean age of 63 years (range 53 – 72 years), but the change was considered not likely to be clinically significant. In a multiple dose study (300 mg/day) in 12 patients with a mean age of 82 years (range 67 – 87 years), the mean levels of modafinil in plasma were approximately two times those historically obtained in matched younger subjects. Due to potential effects from the multiple concomitant medications with which most of the patients were being treated, the apparent difference in modafinil pharmacokinetics may not be attributable solely to the effects of aging. However, the results suggest that the clearance of modafinil may be reduced in the elderly [see Dosage and Administration (2.4) and Use in Specific Populations (8.5)] .

Gender

The pharmacokinetics of modafinil are not affected by gender.

Race

The influence of race on the pharmacokinetics of modafinil has not been studied.

Renal Impairment

In a single dose 200 mg modafinil study, severe chronic renal failure (creatinine clearance ≤20 mL/min) did not significantly influence the pharmacokinetics of modafinil, but exposure to modafinil acid (an inactive metabolite) was increased 9-fold.

Hepatic Impairment

The pharmacokinetics and metabolism of modafinil were examined in patients with cirrhosis of the liver (6 men and 3 women). Three patients had stage B or B+ cirrhosis and 6 patients had stage C or C+ cirrhosis (per the Child-Pugh score criteria). Clinically 8 of 9 patients were icteric and all had ascites. In these patients, the oral clearance of modafinil was decreased by about 60% and the steady state concentration was doubled compared to normal patients [see Dosage and Administration (2.3) and Use in Specific Populations (8.6)] .

Drug Interactions

In vitro data demonstrated that modafinil weakly induces CYP1A2, CYP2B6, and possibly CYP3A activities in a concentration-related manner and that CYP2C19 activity is reversibly inhibited by modafinil. In vitro data also demonstrated that modafinil produced an apparent concentration-related suppression of expression of CYP2C9 activity. Other CYP activities did not appear to be affected by modafinil.

Potential Interactions with Drugs That Inhibit, Induce, or Are Metabolized by Cytochrome P450 Isoenzymes and Other Hepatic Enzymes

The existence of multiple pathways for modafinil metabolism, as well as the fact that a non-CYP-related pathway is the most rapid in metabolizing modafinil, suggest that there is a low probability of substantive effects on the overall pharmacokinetic profile of PROVIGIL due to CYP inhibition by concomitant medications. However, due to the partial involvement of CYP3A enzymes in the metabolic elimination of modafinil, coadministration of potent inducers of CYP3A4/5 (e.g., carbamazepine, phenobarbital, rifampin) or inhibitors of CYP3A4/5 (e.g., ketoconazole, erythromycin) could alter the plasma concentrations of modafinil.

The Potential of PROVIGIL to Alter the Metabolism of Other Drugs by Enzyme Induction or Inhibition

- Drugs Metabolized by CYP3A4/5
  - In vitro data demonstrated that modafinil is a weak inducer of CYP3A activity in a concentration-related manner. Therefore, the blood levels and effectiveness of drugs that are substrates for CYP3A enzymes (e.g., steroidal contraceptives, cyclosporine, midazolam, and triazolam) may be reduced after initiation of concomitant treatment with PROVIGIL [see Drug Interactions (7)] .
  - Ethinyl Estradiol - Administration of modafinil to female volunteers once daily at 200 mg/day for 7 days followed by 400 mg/day for 21 days resulted in a mean 11% decrease in mean Cmaxand 18% decrease in mean AUC0-24of ethinyl estradiol (EE2; 0.035 mg; administered orally with norgestimate). There was no apparent change in the elimination rate of ethinyl estradiol.
  - Triazolam - In the drug interaction study between PROVIGIL and ethinyl estradiol (EE2), on the same days as those for the plasma sampling for EE2pharmacokinetics, a single dose of triazolam (0.125 mg) was also administered. Mean Cmaxand AUC0-∞of triazolam were decreased by 42% and 59%, respectively, and its elimination half-life was decreased by approximately an hour after the modafinil treatment.
  - Cyclosporine - One case of an interaction between modafinil and cyclosporine, a substrate of CYP3A4, has been reported in a 41 year old woman who had undergone an organ transplant. After one month of administration of 200 mg/day of modafinil, cyclosporine blood levels were decreased by 50%. The interaction was postulated to be due to the increased metabolism of cyclosporine, since no other factor expected to affect the disposition of the drug had changed.
  - Midazolam - In a clinical study, concomitant administration of armodafinil 250 mg resulted in a reduction in systemic exposure to midazolam by 32% after a single oral dose (5 mg) and 17% after a single intravenous dose (2 mg).
  - Quetiapine - In a separate clinical study, concomitant administration of armodafinil 250 mg with quetiapine (300 mg to 600 mg daily doses) resulted in a reduction in the mean systemic exposure of quetiapine by approximately 29%.

- Drugs Metabolized by CYP1A2
  - In vitro data demonstrated that modafinil is a weak inducer of CYP1A2 in a concentration-related manner. However, in a clinical study with armodafinil using caffeine as a probe substrate, no significant effect on CYP1A2 activity was observed.
- Drugs Metabolized by CYP2B6
  - In vitro data demonstrated that modafinil is a weak inducer of CYP2B6 activity in a concentration-related manner.
- Drugs Metabolized by CYP2C9
  - In vitro data demonstrated that modafinil produced an apparent concentration-related suppression of expression of CYP2C9 activity suggesting that there is a potential for a metabolic interaction between modafinil and the substrates of this enzyme (e.g., S-warfarin and phenytoin) [see Drug Interactions (7)] .
  - Warfarin: Concomitant administration of modafinil with warfarin did not produce significant changes in the pharmacokinetic profiles of R- and S-warfarin. However, since only a single dose of warfarin was tested in this study, an interaction cannot be ruled out [see Drug Interactions (7)] .
- Drugs Metabolized by CYP2C19
  - In vitro data demonstrated that modafinil is a reversible inhibitor of CYP2C19 activity. CYP2C19 is also reversibly inhibited, with similar potency, by a circulating metabolite, modafinil sulfone. Although the maximum plasma concentrations of modafinil sulfone are much lower than those of parent modafinil, the combined effect of both compounds could produce sustained partial inhibition of the enzyme. Therefore, exposure to some drugs that are substrates for CYP2C19 (e.g., phenytoin, diazepam, propranolol, omeprazole, and clomipramine) may be increased when used concomitantly with PROVIGIL [see Drug Interactions (7)] .
  - In a clinical study, concomitant administration of armodafinil 400 mg resulted in a 40% increase in exposure to omeprazole after a single oral dose (40 mg), as a result of moderate inhibition of CYP2C19 activity.
- Interactions with CNSActive Drugs
  - Concomitant administration of modafinil with methylphenidate or dextroamphetamine produced no significant alterations on the pharmacokinetic profile of modafinil or either stimulant, even though the absorption of modafinil was delayed for approximately one hour.
  - Concomitant modafinil or clomipramine did not alter the pharmacokinetic profile of either drug; however, one incident of increased levels of clomipramine and its active metabolite desmethylclomipramine was reported in a patient with narcolepsy during treatment with modafinil.
  - CYP2C19 also provides an ancillary pathway for the metabolism of certain tricyclic antidepressants (e.g., clomipramine and desipramine) and selective serotonin reuptake inhibitors that are primarily metabolized by CYP2D6. In tricyclic-treated patients deficient in CYP2D6 (i.e., those who are poor metabolizers of debrisoquine; 7-10% of the Caucasian population; similar or lower in other populations), the amount of metabolism by CYP2C19 may be substantially increased. PROVIGIL may cause elevation of the levels of the tricyclics in this subset of patients [see Drug Interactions (7)] .
  - Concomitant administration of armodafinil with quetiapine reduced the systemic exposure of quetiapine.
- Interaction with P-Glycoprotein
  - An in vitro study demonstrated that armodafinil is a substrate of P-glycoprotein. The impact of inhibition of P-glycoprotein is not known.

13 NONCLINICAL TOXICOLOGY

13.1 Carcinogenesis, Mutagenesis, Impairment of Fertility

Carcinogenesis

Carcinogenicity studies were conducted in which modafinil (a mixture of R- and S-modafinil) was administered in the diet to mice for 78 weeks and to rats for 104 weeks at doses of 6, 30, and 60 mg/kg/day. The highest doses studied were associated with plasma modafinil exposures (AUC) less than that in humans at the recommended human dose (RHD) of PROVIGIL (200 mg/day). There was no evidence of tumorigenesis associated with modafinil administration in these studies. However, the mouse study was inadequate because the high dose was not a maximum tolerated dose (MTD). In a mouse carcinogenicity study in which armodafinil (the R-enantiomer of modafinil) was administered at oral doses of up to 300 mg/kg/day in males and 100 mg/kg/day in females for approximately 2 years, no tumorigenic effects were observed. The highest doses studied, which were considered MTDs, were associated with plasma armodafinil exposures less than (females) or 2 times (males) that in humans at the RHD of PROVIGIL.

Mutagenesis

Modafinil was negative in a series of in vitro (i.e., bacterial reverse mutation, mouse lymphoma tk, chromosomal aberration in human lymphocytes, cell transformation in BALB/3T3 mouse embryo cells) or in vivo (mouse bone marrow micronucleus) assays.

Impairment of Fertility

Oral administration of modafinil (doses of up to 480 mg/kg/day) to male and female rats prior to and throughout mating, and continuing in females through day 7 of gestation produced an increase in the time to mate at the highest dose; no effects were observed on other fertility or reproductive parameters. The no-effect dose of 240 mg/kg/day was associated with a plasma modafinil AUC less than that in humans at the RHD of PROVIGIL.

14 CLINICAL STUDIES

14.1 Narcolepsy

The effectiveness of PROVIGIL in improving wakefulness in adult patients with excessive sleepiness associated with narcolepsy was established in two US 9‑week, multi-center, placebo‑controlled, parallel-group, double‑blind studies of outpatients who met the criteria for narcolepsy. A total of 558 patients were randomized to receive PROVIGIL 200 or 400 mg/day, or placebo. The criteria for narcolepsy include either: 1) recurrent daytime naps or lapses into sleep that occur almost daily for at least three months, plus sudden bilateral loss of postural muscle tone in association with intense emotion (cataplexy); or 2) a complaint of excessive sleepiness or sudden muscle weakness with associated features: sleep paralysis, hypnagogic hallucinations, automatic behaviors, disrupted major sleep episode; and polysomnography demonstrating one of the following: sleep latency less than 10 minutes or rapid eye movement (REM) sleep latency less than 20 minutes. For entry into these studies, all patients were required to have objectively documented excessive daytime sleepiness, via a Multiple Sleep Latency Test (MSLT) with two or more sleep onset REM periods and the absence of any other clinically significant active medical or psychiatric disorder. The MSLT, an objective polysomnographic assessment of the patient’s ability to fall asleep in an unstimulating environment, measured latency (in minutes) to sleep onset averaged over 4 test sessions at 2-hour intervals. For each test session, the subject was told to lie quietly and attempt to sleep. Each test session was terminated after 20 minutes if no sleep occurred or 15 minutes after sleep onset.

In both studies, the primary measures of effectiveness were: 1) sleep latency, as assessed by the Maintenance of Wakefulness Test (MWT); and 2) the change in the patient’s overall disease status, as measured by the Clinical Global Impression of Change (CGI-C). For a successful trial, both measures had to show statistically significant improvement.

The MWT measures latency (in minutes) to sleep onset averaged over 4 test sessions at 2 hour intervals following nocturnal polysomnography. For each test session, the subject was asked to attempt to remain awake without using extraordinary measures. Each test session was terminated after 20 minutes if no sleep occurred or 10 minutes after sleep onset. The CGI-C is a 7-point scale, centered at No Change, and ranging from Very Much Worseto Very Much Improved. Patients were rated by evaluators who had no access to any data about the patients other than a measure of their baseline severity. Evaluators were not given any specific guidance about the criteria they were to apply when rating patients.

Both studies demonstrated improvement in objective and subjective measures of excessive daytime sleepiness for both the 200 mg and 400 mg doses compared to placebo. Patients treated with PROVIGIL showed a statistically significantly enhanced ability to remain awake on the MWT at each dose compared to placebo at final visit (Table 2). A statistically significantly greater number of patients treated with PROVIGIL at each dose showed improvement in overall clinical condition as rated by the CGI-C scale at final visit (Table 3).

Nighttime sleep measured with polysomnography was not affected by the use of PROVIGIL.

14.2 Obstructive Sleep Apnea (OSA)

The effectiveness of PROVIGIL in improving wakefulness in patients with excessive sleepiness associated with OSA was established in two multi-center, placebo-controlled clinical studies of patients who met the criteria for OSA. The criteria include either: 1) excessive sleepiness or insomnia, plus frequent episodes of impaired breathing during sleep, and associated features such as loud snoring, morning headaches and dry mouth upon awakening; or 2) excessive sleepiness or insomnia and polysomnography demonstrating one of the following: more than five obstructive apneas, each greater than 10 seconds in duration, per hour of sleep and one or more of the following: frequent arousals from sleep associated with the apneas, bradytachycardia, and arterial oxygen desaturation in association with the apneas. In addition, for entry into these studies, all patients were required to have excessive sleepiness as demonstrated by a score ≥10 on the Epworth Sleepiness Scale (ESS), despite treatment with continuous positive airway pressure (CPAP). Evidence that CPAP was effective in reducing episodes of apnea/hypopnea was required along with documentation of CPAP use.

In the first study, a 12-week trial, a total of 327 patients with OSA were randomized to receive PROVIGIL 200 mg/day, PROVIGIL 400 mg/day, or matching placebo. The majority of patients (80%) were fully compliant with CPAP, defined as CPAP use greater than 4 hours/night on > 70% of nights. The remainder were partially CPAP compliant, defined as CPAP use < 4 hours/night on >30% of nights. CPAP use continued throughout the study. The primary measures of effectiveness were 1) sleep latency, as assessed by the Maintenance of Wakefulness Test (MWT) and 2) the change in the patient’s overall disease status, as measured by the Clinical Global Impression of Change (CGI-C) at the final visit [ see Clinical Studies (14.1) for a description of these measures].

Patients treated with PROVIGIL showed a statistically significant improvement in the ability to remain awake compared to placebo-treated patients as measured by the MWT at final visit (Table 2). A statistically significant greater number of patients treated with PROVIGIL showed improvement in overall clinical condition as rated by the CGI-C scale at final visit (Table 3). The 200 mg and 400 mg doses of PROVIGIL produced statistically significant effects of similar magnitude on the MWT, and also on the CGI-C.

In the second study, a 4-week trial, 157 patients with OSA were randomized to receive PROVIGIL 400 mg/day or placebo. Documentation of regular CPAP use (at least 4 hours/night on 70% of nights) was required for all patients. The primary measure of effectiveness was the change from baseline on the ESS at final visit. The baseline ESS scores for the PROVIGIL and placebo groups were 14.2 and 14.4, respectively. At week 4, the ESS was reduced by 4.6 in the PROVIGIL group and by 2.0 in the placebo group, a difference that was statistically significant.

Nighttime sleep measured with polysomnography was not affected by the use of PROVIGIL.

14.3 Shift Work Disorder (SWD)

The effectiveness of PROVIGIL in improving wakefulness in patients with excessive sleepiness associated with SWD was demonstrated in a 12-week placebo-controlled clinical trial. A total of 209 patients with chronic SWD were randomized to receive PROVIGIL 200 mg/day or placebo. All patients met the criteria for chronic SWD. The criteria include: 1) either, a) a primary complaint of excessive sleepiness or insomnia which is temporally associated with a work period (usually night work) that occurs during the habitual sleep phase, or b) polysomnography and the MSLT demonstrate loss of a normal sleep-wake pattern (i.e., disturbed chronobiological rhythmicity); and 2) no other medical or mental disorder accounts for the symptoms, and 3) the symptoms do not meet criteria for any other sleep disorder producing insomnia or excessive sleepiness (e.g., time zone change [jet lag] syndrome).

It should be noted that not all patients with a complaint of sleepiness who are also engaged in shift work meet the criteria for the diagnosis of SWD. In the clinical trial, only patients who were symptomatic for at least 3 months were enrolled.

Enrolled patients were also required to work a minimum of 5 night shifts per month, have excessive sleepiness at the time of their night shifts (MSLT score < 6 minutes), and have daytime insomnia documented by a daytime polysomnogram.

The primary measures of effectiveness were 1) sleep latency, as assessed by the MSLT performed during a simulated night shift at the final visit and 2) the change in the patient’s overall disease status, as measured by the CGI-C at the final visit [ see Clinical Studies (14.1) for a description of these measures.].

Patients treated with PROVIGIL showed a statistically significant prolongation in the time to sleep onset compared to placebo-treated patients, as measured by the nighttime MSLT at final visit (Table 2). A statistically significant greater number of patients treated with PROVIGIL showed improvement in overall clinical condition as rated by the CGI-C scale at final visit (Table 3).

Daytime sleep measured with polysomnography was not affected by the use of PROVIGIL.

Table 2. Average Baseline Sleep Latency and Change from Baseline at Final Visit (MWT and MSLT in minutes)
Disorder | Measure | PROVIGIL; 200 mg [Significantly different than placebo for all trials (p<0.01 for all trials but SWD, which was p<0.05)] |  | PROVIGIL; 400 mg |  | Placebo
 |  | Baseline | Change from Baseline | Baseline | Change from Baseline | Baseline | Change from Baseline
Narcolepsy I | MWT | 5.8 | 2.3 | 6.6 | 2.3 | 5.8 | -0.7
Narcolepsy II | MWT | 6.1 | 2.2 | 5.9 | 2.0 | 6.0 | -0.7
OSA | MWT | 13.1 | 1.6 | 13.6 | 1.5 | 13.8 | -1.1
SWD | MSLT | 2.1 | 1.7 | - | - | 2.0 | 0.3

Table 3. Clinical Global Impression of Change (CGI-C) (Percent of Patients Who Improved at Final Visit)
Disorder | PROVIGIL; 200 mg [Significantly different than placebo for all trials (p<0.01)] | PROVIGIL; 400 mg | Placebo
Narcolepsy I | 64% | 72% | 37%
Narcolepsy II | 58% | 60% | 38%
OSA | 61% | 68% | 37%
SWD | 74% | ------ | 36%

16 HOW SUPPLIED/STORAGE AND HANDLING

16.1 How Supplied

PROVIGIL® (modafinil) tablets are available as follows:

100 mg: Each capsule-shaped, white to off white tablet is debossed with "PROVIGIL" on one side and "100 MG" on the other.

NDC 60429-009-30 – Bottles of 30

200 mg: Each capsule-shaped, white to off white, scored tablet is debossed with "PROVIGIL" on one side and "200 MG" on the other.

NDC 60429-010-30 – Bottles of 30

16.2 Storage

Store at 20oC ‑ 25oC (68oF ‑ 77oF).

17 PATIENT COUNSELING INFORMATION

Advise the patient to read the FDA-approved patient labeling (Medication Guide).

Allergic Reactions

Advise patients to stop taking PROVIGIL and to notify their physician right away if they develop a rash, hives, mouth sores, blisters, peeling skin, trouble swallowing or breathing, or a related allergic phenomenon.

Driving and Dangerous Activities

Advise patients not to alter their previous behavior with regard to potentially dangerous activities (e.g., driving, operating machinery) or other activities requiring appropriate levels of wakefulness, until and unless treatment with PROVIGIL has been shown to produce levels of wakefulness that permit such activities. Advise patients that PROVIGIL is not a replacement for sleep.

Continuing Previously Prescribed Treatments

Inform patients that it may be critical that they continue to take their previously prescribed treatments (e.g., patients with OSA receiving CPAP should continue to do so).

Discontinuing Drug Due to Adverse Reactions

Advise patients to stop taking PROVIGIL and contact their physician right away if they experience chest pain, rash, depression, anxiety, or signs of psychosis or mania.

Pregnancy

Advise patients to notify their physician if they become pregnant or intend to become pregnant during therapy. Caution patients regarding the potential increased risk of pregnancy when using steroidal contraceptives (including depot or implantable contraceptives) with PROVIGIL and for one month after discontinuation of therapy.

Nursing

Advise patients to notify their physician if they are breastfeeding an infant.

Concomitant Medication

Advise patients to inform their physician if they are taking, or plan to take, any prescription or over‑the‑counter drugs, because of the potential for interactions between PROVIGIL and other drugs.

Alcohol

Advise patients that the use of PROVIGIL in combination with alcohol has not been studied. Advise patients that it is prudent to avoid alcohol while taking PROVIGIL.

Dispense with Medication Guide available at https://gsms.us/

Manufactured for:
Apotex Corp.
Weston, Florida

33326 USA

All rights reserved.
ApoPharma is a registered trademark of Apotex Inc.

Marketed by:
GSMS, Inc.
Camarillo, CA 93012 USA

MEDICATION GUIDE

PROVIGIL®(pro-vij-el) C-IV
(modafinil)
Tablets

Medication Guide available at https://gsms.us/

Read this Medication Guide before you start taking PROVIGIL and each time you get a refill. There may be new information. This information does not take the place of talking with your doctor about your medical condition or treatment.

What is the most important information I should know about PROVIGIL?

PROVIGIL may cause serious side effects including a serious rash or a serious allergic reaction that may affect parts of your body such as your liver or blood cells. Any of these may need to be treated in a hospital and may be life-threatening.

Stop taking PROVIGIL and call your doctor right away or get emergency help if you have any of these symptoms:

- skin rash, hives, sores in your mouth, or your skin blisters and peels
- swelling of your face, eyes, lips, tongue, or throat
- trouble swallowing or breathing
- fever, shortness of breath, swelling of the legs, yellowing of the skin or whites of the eyes, or dark urine

If you have a severe rash with PROVIGIL, stopping the medicine may not keep the rash from becoming life-threatening or causing you to be permanently disabled or disfigured.

PROVIGIL is not approved for use in children for any medical condition.

It is not known if PROVIGIL is safe or effective in children under 17 years of age.

What is PROVIGIL?

PROVIGIL is a prescription medicine used to improve wakefulness in adults who are very sleepy due to one of the following diagnosed sleep disorders:

- narcolepsy
- obstructive sleep apnea (OSA). PROVIGIL is used to treat excessive sleepiness, but not the obstruction or medical condition that is causing OSA. You should talk with your doctor about treatments for OSA before you start taking PROVIGIL and during treatment with PROVIGIL. PROVIGIL does not take the place of treatments that your doctor has prescribed for OSA. It is important that you continue to use these treatments as prescribed by your doctor.
- shift work disorder (SWD)

PROVIGIL will not cure these sleep disorders. PROVIGIL may help the sleepiness caused by these conditions, but it may not stop all your sleepiness. PROVIGIL does not take the place of getting enough sleep. Follow your doctor's advice about good sleep habits and using other treatments.

PROVIGIL is a federally controlled substance (C-IV) because it can be abused or lead to dependence. Keep PROVIGIL in a safe place to prevent misuse and abuse. Selling or giving away PROVIGIL may harm others, and is against the law. Tell your doctor if you have ever abused or been dependent on alcohol, prescription medicines, or street drugs.

Who should not take PROVIGIL?

Do not take PROVIGIL if you:

- are allergic or developed a rash to modafinil or armodafinil (NUVIGIL®) or any of the ingredients in PROVIGIL. See the end of this Medication Guide for a complete list of ingredients in PROVIGIL.

What should I tell my doctor before taking PROVIGIL?

Tell your doctor about all of your medical conditions including, if you:

- have a history of mental health problems, including psychosis
- have heart problems or had a heart attack
- have high blood pressure. Your blood pressure may need to be checked more often while taking PROVIGIL.
- have liver or kidney problems
- have a history of drug or alcohol abuse or addiction
- are pregnant or planning to become pregnant. It is not known if PROVIGIL will harm your unborn baby.
  Pregnancy Registry: There is a registry for women who become pregnant during treatment with PROVIGIL. The purpose of this registry is to collect information about the safety of PROVIGIL during pregnancy. Contact the registry as soon as you learn that you are pregnant, or ask your doctor to contact the registry for you. You or your doctor can get information and enroll you in the registry by calling 1-866-404-4106.
- are breastfeeding. It is not known if PROVIGIL passes into your breast milk. Talk to your doctor about the best way to feed your baby if you take PROVIGIL.

Tell your doctor about all the medicines you take, including prescription and over-the-counter medicines, vitamins, and herbal supplements. PROVIGIL and many other medicines can interact with each other, sometimes causing side effects. PROVIGIL may affect the way other medicines work, and other medicines may affect how PROVIGIL works. Your dose of PROVIGIL or certain other medicines may need to be changed.

Especially, tell your doctor if you use or take:

- a hormonal birth control method, such as birth control pills, shots, implants, patches, vaginal rings, and intrauterine devices (IUDs). Hormonal birth control methods may not work while you take PROVIGIL. Women who use one of these methods of birth control may have a higher chance for getting pregnant while taking PROVIGIL, and for one month after stopping PROVIGIL. Talk to your doctor about birth control choices that are right for you while taking PROVIGIL.

Know the medicines you take. Keep a list of them and show it to your doctor and pharmacist when you get a new medicine. Your doctor or pharmacist will tell you if it is safe to take PROVIGIL and other medicines together. Do not start any new medicines with PROVIGIL unless your doctor has told you it is okay.

How should I take PROVIGIL?

- Take PROVIGIL exactly as prescribed by your doctor. Your doctor will prescribe the dose of PROVIGIL that is right for you. Do not change your dose of PROVIGIL without talking to your doctor.
- Your doctor will tell you the right time of day to take PROVIGIL.
  - People with narcolepsy or OSA usually take PROVIGIL 1 time each day in the morning.
  - People with SWD usually take PROVIGIL about 1 hour before their work shift.
- Do not change the time of day you take PROVIGIL unless you have talked to your doctor. If you take PROVIGIL too close to your bedtime, you may find it harder to go to sleep.
- You can take PROVIGIL with or without food.
- If you take more than your prescribed dose or if you take an overdose of PROVIGIL, call your doctor or go to the nearest hospital emergency room right away.

Symptoms of an overdose of PROVIGIL may include:

- trouble sleeping
- restlessness
- confusion
- feeling disoriented
- feeling excited
- hearing, seeing, feeling, or sensing things that are not really there (hallucinations)
- nausea and diarrhea
- a fast or slow heartbeat
- chest pain
- increased blood pressure

What should I avoid while taking PROVIGIL?

- Do not drive a car or do other dangerous activities until you know how PROVIGIL affects you. People with sleep disorders should always be careful about doing things that could be dangerous. Do not change your daily habits until your doctor tells you it is okay.
- You should avoid drinking alcohol. It is not known how drinking alcohol will affect you when taking PROVIGIL.

What are possible side effects of PROVIGIL?

PROVIGIL may cause serious side effects.Stop taking PROVIGIL and call your doctor right away or get emergency help if you get any of the following:

- a serious rash or serious allergic reaction. (See “What is the most important information I should know about PROVIGIL?”)
- mental (psychiatric) symptoms, including:
  - depression
  - feeling anxious
  - hearing, seeing, feeling, or sensing things that are not really there (hallucinations)
  - an extreme increase in activity and talking (mania)
  - thoughts of suicide
  - aggressive behavior
  - other mental problems
- symptoms of a heart problem,including chest pain, abnormal heartbeat, and trouble breathing.

Common side effects that can happen in anyone who takes PROVIGIL include:

- headache

- diarrhea

- back pain

- feeling anxious

- nausea

- trouble sleeping

- feeling nervous

- dizziness

- stuffy nose

- upset stomach

PROVIGIL is not approved for use in childrenfor any medical condition including Attention Deficit Hyperactivity Disorder (ADHD). In studies of PROVIGIL in children with narcolepsy, side effects included:

- Tourette’s syndrome
- hostile behavior
- increase in sudden loss of muscle tone and severe muscle weakness
- increase in seeing and hearing things when falling asleep
- increase in suicidal thoughts
- low white blood count
- painful menstrual periods

Tell your doctor if you get any side effect that bothers you or that does not go away while taking PROVIGIL.

These are not all the side effects of PROVIGIL. For more information, ask your doctor or pharmacist.

Some effects of PROVIGIL on the brain are the same as other medicines called “stimulants”. These effects may lead to abuse or dependence on PROVIGIL.

Call your doctor for medical advice about side effects. You may report side effects to FDA at 1-800-FDA-1088.

How should I store PROVIGIL?

- Store PROVIGIL at room temperature between 68°F and 77°F (20°C and 25°C).
- Keep PROVIGIL and all medicines out of the reach of children.

General information about the safe and effective use of PROVIGIL.

Medicines are sometimes prescribed for purposes other than those listed in a Medication Guide. Do not use PROVIGIL for a condition for which it was not prescribed. Do not give PROVIGIL to other people, even if they have the same symptoms you have. It may harm them and it is against the law.

This Medication Guide summarizes the most important information about PROVIGIL. If you would like more information, talk with your doctor. You can ask your doctor or pharmacist for information about PROVIGIL that is written for health professionals. For more information, call 1-800-706-5575

What are the ingredients in PROVIGIL?

Active Ingredient:modafinil

Inactive Ingredients:lactose monohydrate, microcrystalline cellulose, pregelatinized starch, croscarmellose sodium, povidone, and magnesium stearate.

Manufactured for:
Apotex Corp.
Weston, Florida

33326 USA

This Medication Guide has been approved by the U.S. Food and Drug Administration.

All rights reserved

ApoPharma is a registered trademark of Apotex Inc.

Revised: February 2025

Marketed by:
GSMS, Inc.
Camarillo, CA 93012 USA

Package/Label Display Panel

NDC 60429-009-30
30 Tablets
PROVIGIL® (MODAFINIL) CIV 100 mg
Medication Guide Required: Each time PROVIGIL is dispensed, give the patient a Medication Guide.
Rx only

Package/Label Display Panel

NDC 60429-010-30
30 Tablets
PROVIGIL® (MODAFINIL) CIV 200 mg
Medication Guide Required: Each time PROVIGIL is dispensed, give the patient a Medication Guide.
Rx only